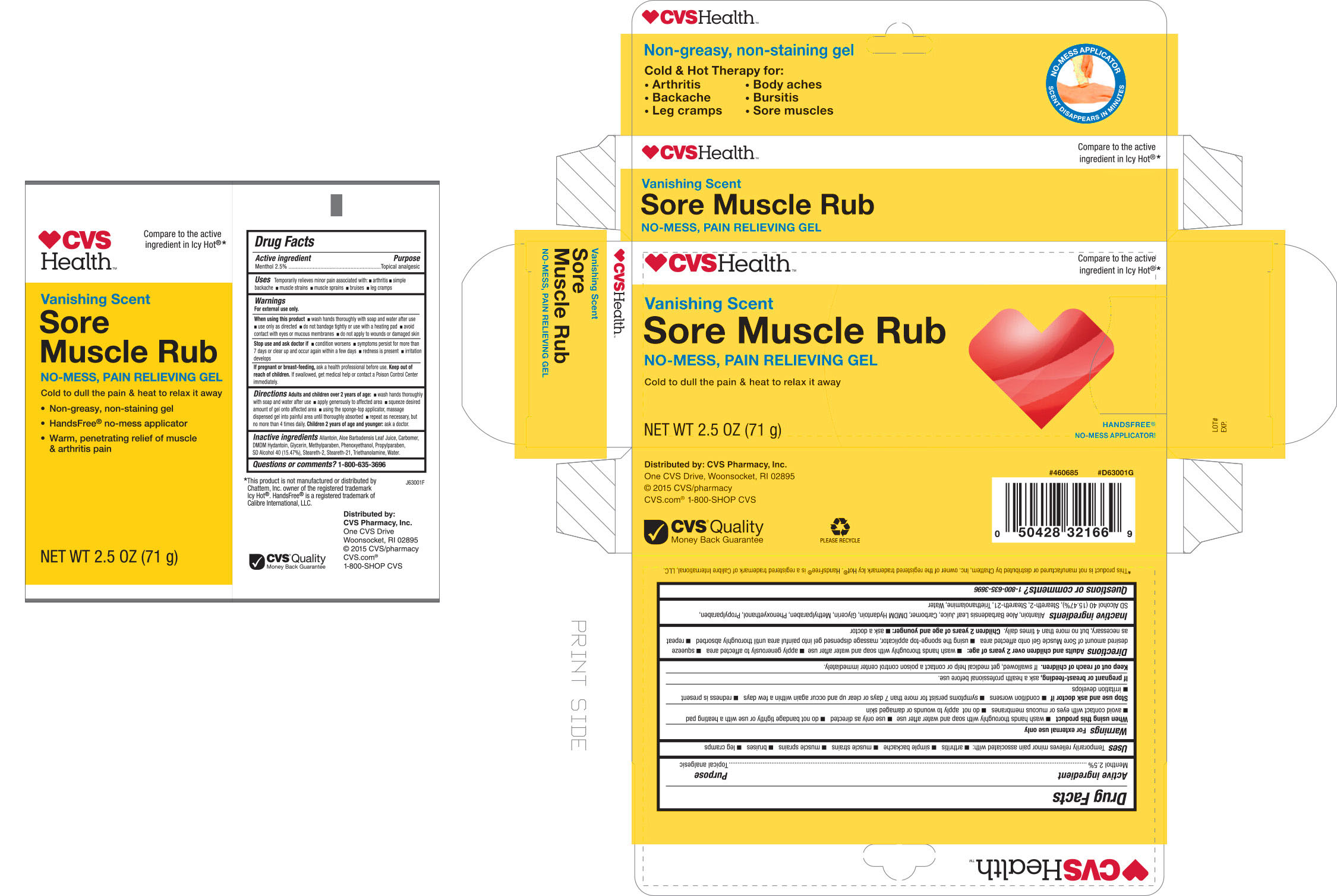 DRUG LABEL: CVS Sore Muscle Rub
NDC: 69842-712 | Form: CREAM
Manufacturer: CVS Pharmacy
Category: otc | Type: HUMAN OTC DRUG LABEL
Date: 20170104

ACTIVE INGREDIENTS: MENTHOL 0.025 g/1 g
INACTIVE INGREDIENTS: ALLANTOIN; ALOE VERA LEAF; CARBOMER INTERPOLYMER TYPE A (ALLYL SUCROSE CROSSLINKED); DMDM HYDANTOIN; GLYCERIN; METHYLPARABEN; PHENOXYETHANOL; PROPYLPARABEN; ALCOHOL; STEARETH-2; STEARETH-21; TROLAMINE; WATER

Drug Facts

Active Ingredient

Menthol 2.5%

Purpose

Topical Analgesic

Uses

Temporarily relives minor pain associated with:

- arthritis
- simple backache
- muscle strains
- muscle sprains
- bruises
- cramps

WARNINGS

For external use only

When using this product

- Use only as directed
- wash hand thoroughly with soap and water after use
- do not bandage tightly or use with a heating pad
- avoid contact with eyes or mucous membranes
- do not apply to wounds or damaged skin

Stop use and ask doctor if

- Condition worsens
- symptoms persist for more than 7 days or clear up and occur again within a few days
- redness is present
- irritation develops

If pregnant or breast-feeding

ask a health care professional before use.

KEEP OUT OF REACH OF CHILDREN

If swallowed, get medical help or contact a poison control center immediately.

Directions

Adults and children over 2 years:

- wash hand thoroughly with soap and water after use
- apply generously to affected area
- squeeze desired amount of gel onto affected area
- using the sponge-top applicator, massage dispensed gel into painful area until thoroughly absorbed
- repeat as necessary, but no more than 4 times daily

Children 2 years or younger:

- Ask a doctor

INACTIVE INGREDIENT

Allantoin, Aloe Barbadensis Leaf Juice, Carbomer, DMDM Hydantoin, Glycerin, Methylparaben, Phenoxyethanol, Propylparaben, SD Alcohol 40 (15.47%), Steareth-2, steareth-21, Triethanolamine, water.

Questions or comments

1-800-635-3696